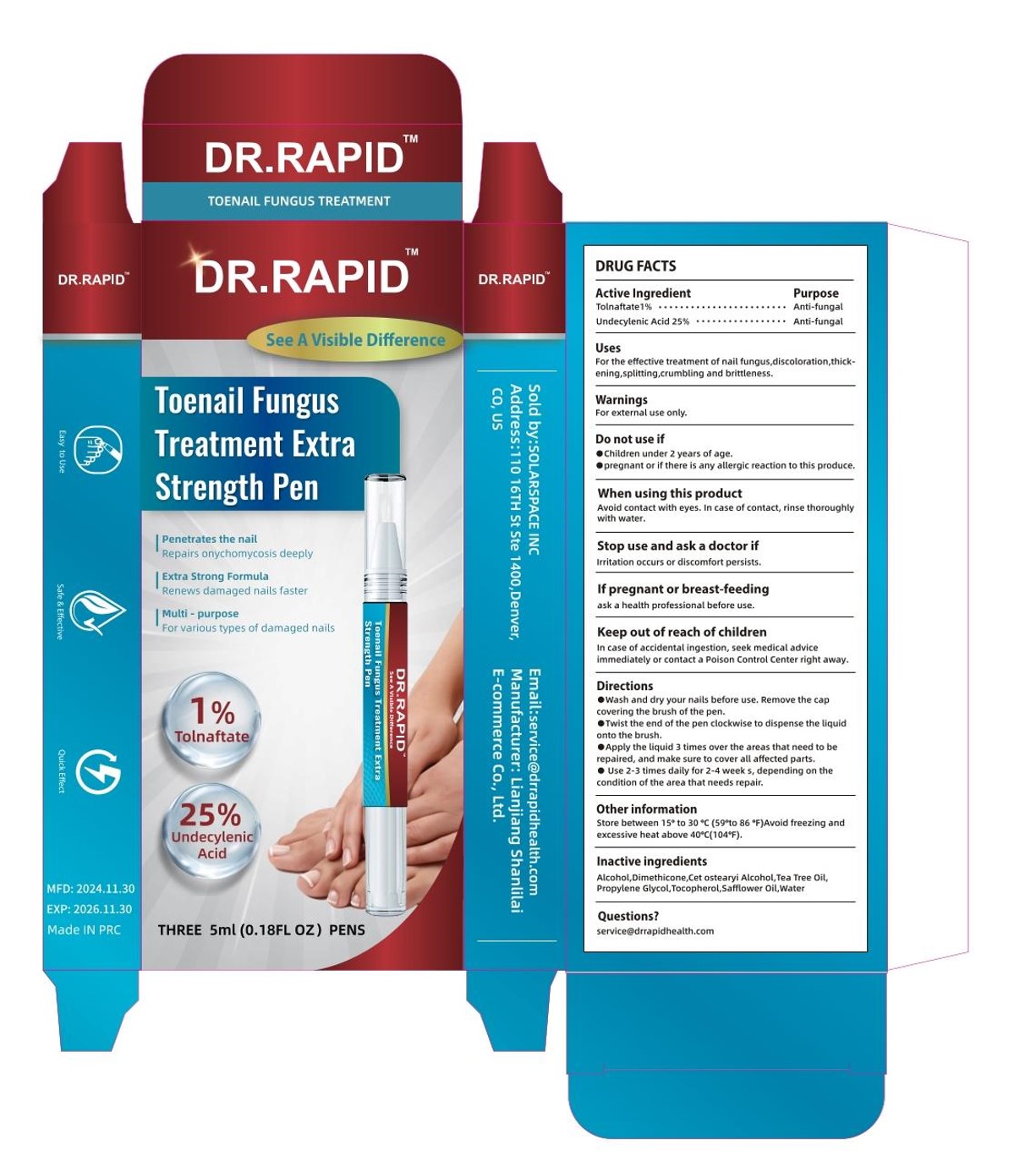 DRUG LABEL: Toenail Fungus Treatment Extra Strength Pen
NDC: 85038-001 | Form: LIQUID
Manufacturer: Lianjiang Shanlilai E-commerce Co., Ltd.
Category: otc | Type: HUMAN OTC DRUG LABEL
Date: 20241211

ACTIVE INGREDIENTS: TOLNAFTATE 1 g/100 mL; UNDECYLENIC ACID 25 g/100 mL
INACTIVE INGREDIENTS: TOCOPHEROL; SAFFLOWER OIL; WATER; PROPYLENE GLYCOL; ALCOHOL; TEA TREE OIL; DIMETHICONE; CETOSTEARYL ALCOHOL

Toenail Fungus Treatment Extra Strength Pen

Toenail Fungus Treatment Extra Strength Pen

ACTIVE INGREDIENT

TOLNAFTATE 1%
UNDECYLENIC ACID 25%

PURPOSE

Anti-fungal

INDICATIONS AND USAGE

For the effective treatment of nail fungus,discoloration,thick-ening,splitting,crumbling and brittleness.

WARNINGS

For external use only.

DO NOT USE

children under 2 years of age.
pregnant or if there is any allergic reaction to this produce.

WHEN USING

Avoid contact with eyes. in case of contact, rinse thoroughly
with water.

STOP USE

lrritation occurs or discomfort persists.

KEEP OUT OF REACH OF CHILDREN

In case of accidental ingestion, seek medical advice
immediately or contact a Poison Control center right away.

DOSAGE AND ADMINISTRATION

Wash and dry your nails before use, Remove the capcovering the brush of the pen.
Twist the end of the pen clockwise to dispense the liquidonto the brush.
Apply the liquid 3 times over the areas that need to berepalred, and make sure to cover all affected parts.
Use 2-3 times daily for 2-4 week s, depending on thecondition of the area that needs repair.

STORAGE AND HANDLING

Store between 15° to 30 °C (59 °to 86 °F)Avoid freezing andexcessive heat above 40C°(104F).

INACTIVE INGREDIENT

ALCOHOL
DIMETHICONE
CETOSTEARYL ALCOHOL
TEA TREE OIL
PROPYLENE GLYCOL
TOCOPHEROL
SAFFLOWER OIL
WATER